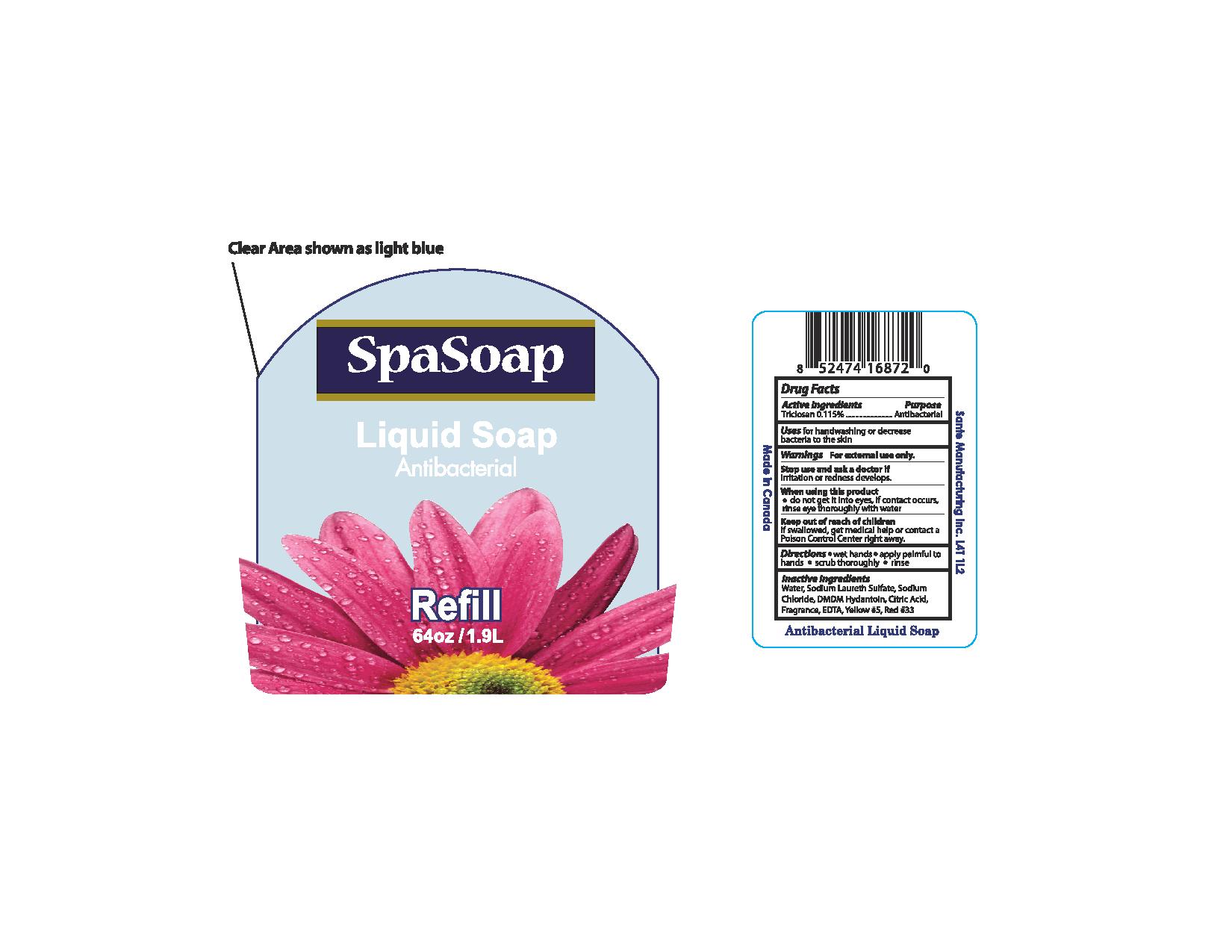 DRUG LABEL: Antibacterial
NDC: 71020-008 | Form: LIQUID
Manufacturer: Sante Manufacturing Inc
Category: otc | Type: HUMAN OTC DRUG LABEL
Date: 20161026

ACTIVE INGREDIENTS: TRICLOSAN 1.15 mg/1 mL
INACTIVE INGREDIENTS: WATER; SODIUM LAURETH SULFATE; SODIUM CHLORIDE; DMDM HYDANTOIN; ANHYDROUS CITRIC ACID; EDETIC ACID; FD&C YELLOW NO. 5; FD&C RED NO. 3

Active Ingredient - Triclosan 0.115%

Purpose - Antibacterial

INDICATIONS AND USAGE

Uses for handwashing to decrease bacteria on the skin

WARNINGS

Warning for external use only

STOP USE

Stop us and ask a doctor if irritation or redness develops

When using this product do not get into eyes. If contact occurs, rinse eye thoroughly with water

Keep out of reach of children. If swallowed, get medical help or contact a Poison Control Center right away

Directions

- Wet Hands
- apply palmful to hands
- scrub thoroughly
- rinse

INACTIVE INGREDIENT

Water, Sodium Laureth Sulfate, Sodium Chloride, DMDM Hydantoin, Citric Acid, Fragrance, EDTA, Yellow#5, Red# 33